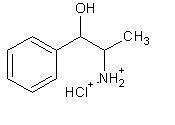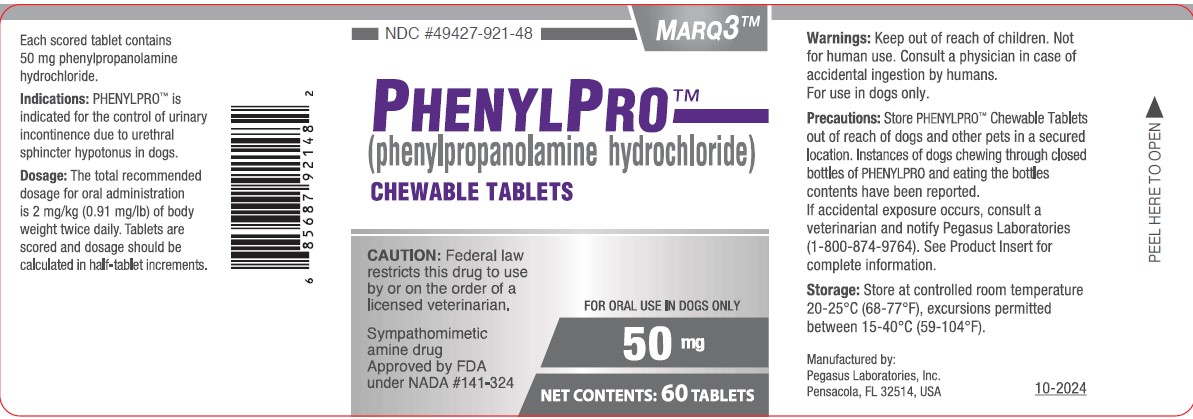 DRUG LABEL: PhenylPro 50
NDC: 49427-921 | Form: TABLET, CHEWABLE
Manufacturer: Pegasus Laboratories, Inc.
Category: animal | Type: PRESCRIPTION ANIMAL DRUG LABEL
Date: 20251229

ACTIVE INGREDIENTS: PHENYLPROPANOLAMINE HYDROCHLORIDE 50 1/1 1

For oral use in dogs only

Caution: Federal law restricts this drug to use by or on the order of a licensed veterinarian.

Description:

PHENYLPRO (phenylpropanolamine hydrochloride) is a sympathomimetic amine closely related to ephedrine.

Phenylpropanolamine hydrochloride (PPA) is the nonproprietary designation for benzenemethanol, α - (1-aminoethyl) - hydrochloride, (R*,S*) -, (±).

The empirical formula is C9H13NO•HCL and the molecular weight is 187.67. It is a white crystalline compound having a slight aromatic odor.

PPA is freely soluable is water and alcohol but is practically insoluable in ether, benzene and chloroform. The chemical structure of phenylpropanolamine hydrochloride is:

Indication:

PHENYLPRO is indicated for the control of urinary incontinence due to urethral sphincter hypotonus in dogs.

Dosage and Administration:

The total recommended dosage for oral administration is 2 mg/kg (0.91 mg/lb) of body weight twice daily. PHENYLPRO is scored and dosage should be calculated in half-tablet increments.

Warnings:

Not for human use. Keep out of reach of children. Consult a physician in case of accidental ingestion by humans.

Precautions:

PHENYLPRO may cause increased thirst; therefore, provide ample fresh water.

Overdose has been associated with dogs chewing through closed bottles of PHENYLPRO and consuming multiple tablets. Therefore, it is important to store PHENYLPRO Chewable Tablets out of reach of dogs and other pets in a secured location.

Use in dogs with incontinence due to a urinary tract infection will mask symptoms. PHENYLPRO is not effective in dogs with incontinence due to neurologic disease or malformations.

PHENYLPRO may cause hypertension; therefore, use with caution in dogs with pre-existing heart disease, hypertension, liver disease, kidney insufficiency, diabetes, glaucoma, and conditions with a predilection for hypertension. Use with caution in dogs receiving sympathomimetic drugs, tricyclic antidepressants, or monoamine oxidase inhibitors as increased toxicity may result. Use with caution in dogs administered halogenated gaseous anesthetics as this may increase the risk of cardiac arrhythmias.

A laboratory study on human blood revealed that PPA used in conjunction with aspirin may potentiate decreased platelet aggregation.

The safe use of PHENYLRPO in dogs used for breeding purposes, during pregnancy or in lactating bitches has not been evaluated.

Adverse Reactions "Pre Approval Experience":

A placebo-controlled clinical study involving 123 PHYENYLPRO-treated dogs and 61 placebo-treated dogs was conducted for 28 days. The most common adverse reactions are shown in Table 1 below. In addition, one dog exhibited disorientation, nervousness, a 7.7% loss of body weight, and hypertension with proteinuria. A second dog exhibited restless behavior, lethargy, a 2.8% body weight loss and proteinuria.

Table 1: Number and percentage of dogs with adverse reactions in the 28 day placebo-controlled clinical study

Adverse Reactions | PHENYLPRO-Treated (N=123) | Placebo-Treated (N=61)
Emesis | 20.3% | 8.2%
Hypertension (160 mmHg)^1 | 19.5% | 14.7%
Anorexia | 16.3% | 3.3%
Body Weight Loss (>5%)^2 | 16.1% | 6.8%
Proteinuria | 13.0% | 8.2%
Anxiety/aggression/behavior change | 9.7% | 3.2%
Diarrhea | 7.3% | 9.8%
Polydipsia | 6.5% | 9.8%
Lethargy | 5.7% | 1.6%
Musculoskeletal Disorder | 3.2% | 1.6%
Insomnia/sleep disorder | 2.5% | 0.0%

^1 One or more systolic blood pressure readings of 160mmHg.

^2 The "N" for weight loss is PHENYLPRO treated N=118 and placebo N=59 because seven dogs did not have a final weight at the time of withdrawal from the study.

ADVERSE REACTIONS

One-hundred fifty seven dogs continued into the 6-month open label clinical study. The most common adverse reactions are listed in Table 2 below. In addition, one dog exhibited progressively worsening hypertension with proteinuria. Five dogs enrolled in the study with pre-existing heart disease. Of these, one dog developed systolic failure with an unknown relation to treatment.

Table 2: Number and percentage of dogs with adverse reaction in the 6-month open-label clinical study

Adverse Reactions | Total N = 125
Hypertension (≥ 160 mmHg)^1 | 34.6%
Body weight loss (≥ 5%) | 24.8%
Emesis | 19.7%
Proteinuria | 15.3%
Anorexia | 10.2%
Diarrhea | 6.4%
Lethargy | 5.7%
Anxiety/behavior change/aggression | 5.7%

^1 Percent of dogs with systolic blood pressures of ≥ 160 mmHg on day -7 were 30.2% and on day 0 were 33.3%.

POST APPROVAL EXPERIENCE (2015):

The following adverse events are based on voluntary, post approval reporting. Not all adverse events are reported to FDA/CVM. It is not always possible to reliably estimate the adverse event frequency or establish a causal relationship to product exposure using these data. The signs reported are listed in decreasing order of reporting frequency by body system:

Gastrointestinal: Vomiting, anorexia, diarrhea, hypersalivation,

Behavioral: Agitation, lethargy, vocalization, confusion,

General body system: Polydipsia, weight loss, weakness, fever,

Respiratory: Panting,

Dermatological: Erythema, piloerection,

Hepatic: Elevated serum alanine aminotransferase (ALT), elevated serum alkaline phosphatase (ALP),

Neurologic: Ataxia, seizures, tremors,

Renal/Urinary: Renal failure, hematuria, urinary retention,

Cardiovascular: Tachycardia, hypertension, bradycardia, arrhythmias,

Sensory: Ophthalmic disorders, mydriasis and eye redness.

In some cases, death, including euthanasia, has been reported. Sudden death was sometimes preceded by neurologic signs, vocalization, or collapse. A necropsy of one dog revealed subarachnoidal and intraventricular hemorrhage in the brain.

The following signs have been reported more often with a dose higher than the recommended dosage: agitation, arrhythmia, bradycardia, erythema, fever, hypersalivation, hypertension, lethargy, mydriasis, panting, piloerection, tachycardia, tremor, and urinary retention.

For a copy of the Safety Data Sheet (SDS) or to report suspected adverse drug events, contact Pegasus Laboratories at 1-800-874-9764. For additional information about adverse drug experience reporting for animal drugs, contact FDA at 1-888-FDA-VETS or www.fda.gov/reportanimalae.

Information for Owner or Person Treating Animal:

Always follow the dosage instructions for PHENYLPRO provided by your veterinarian. Monitor your dog after giving PHENYLPRO to be sure all of it was consumed. If you have difficulty giving PHENYLPRO, contact your veterinarian.

It may take several days of treatment with PHENYLPRO before urinary incontinence improves. If you miss a dose, give it as soon as you remember. If it is close to the time for the next dose, skip the dose you missed and go back to the regular dosing schedule. Do not give two doses at once. PHENLYPRO should only be given to the dog for which it was prescribed. Because PHENYLPRO is flavored, store in a secure area.

Dogs may willingly consume more than the recommended dosage of PHENYLPRO Chewable Tablets. Instances of dogs chewing through closed bottles of PHENLYPRO and eating the bottle contents have been reported. Keep the product in a secured storage area out of reach of pets in order to prevent accidental ingestion or overdose. Contact your veterinarian immediately if the dog ingests more tablets than prescribed or if other pets ingest PHENYLPRO Chewable Tablets. In the case of accidental ingestion by humans, contact a physician immediately.

Contact your veterinarian if you notice restlessness or irritability, loss of appetite, the incontinence persists or worsens, or any other unusual signs.

Consult your veterinarian before using PHENYLPRO with any other medications.

Clinical Pharmacology:

Phenylpropanolamine is a chemical analogue of the endogenous sympathomimetic amines. It is an alpha-adrenergic agent which has been reported to increase urethral tone in dogs.2 Its mechanism of action is not well determined, but it is believed to cause the release of norepinephrine by indirectly stimulating both the alpha and beta-adrenergic receptors of the smooth muscle to increase smooth muscle tone of the urethra, bladder neck, and the internal urethral sphincter.3, 4

The pharmacokinetics of phenylpropanolamine in dogs has not been well studied. In humans, phenylpropanolamine is readily absorbed after oral administration of solid dosage forms and has an onset of action of approximately 15-30 minutes and duration of effect of about three hours. In a published study in dogs, phenylpropanolamine disposition was characterized in three dogs administered phenylpropanolamine intravenously and orally in immediate-release and controlled-release formulations. 5 The terminal elimination half-life averaged 3.5 ± 0.5 hours after the intravenous dose. Oral absorption from the immediate-release capsule was rapid and bioavailability was 98.2 ± 6.9 percent. Absorption of phenylpropanolamine from the controlled-release dosage form was biphasic; an initial rapid phase was followed by a second, slower absorption phase which continued over 16 hours. Plasma concentrations then declined with a half-life roughly parallel to the intravenous and oral immediate-release half-lives. Oral bioavailability from the controlled-release tablet was 93.7 ± 5.9 percent.

Effectiveness:

A 28-day placebo-controlled clinical study was conducted in 21 study sites across the U.S. The study included 184 dogs with urinary incontinence due to sphincter hypotonus of which 127 dogs (100 female, 27 male) were evaluated for effectiveness. Dogs were randomly assigned either to receive 2mg/kg PHENYLPRO (123 dogs) or placebo (61 dogs) administered twice daily for 28 days. PHENYLPRO was effective in controlling urinary incontinence based on decrease in urinary accidents per week. Changes to hematology and serum chemistry were not considered clinically significant or related to treatment.

Table 3: Mean urinary accidents per week by treatment group, females

Week | Mean Urinary Accidents (PHENYLPRO-treated, N=66) | Mean Urinary Accidents (Placebo, N=34)
Pretreatment | 9.0 | 7.8
1 | 3.9 | 4.8
2 | 2.5 | 4.1
3 | 1.5 | 3.1
4 | 1.6 | 2.8

One-hundred fifty seven dogs continued into the 6-month open label clinical study conducted in 21 study sites across the U.S. All the dogs had participated in the 28-day placebo-controlled clinical study and had urinary incontinence due to sphincter hypotonus. Dogs were administered 2 mg/kg PHENYLPRO orally twice daily for 180 days. PHENYLPRO was effective for the control of urinary incontinence for 180 days based on 98.1% owner satisfaction. The dogs averaged just one accident per dog per week. Changes to hematology and serum chemistry were not considered clinically significant or related to treatment.

The dogs voluntarily consumed 53.9% of the doses and 33.7% of the doses in food. The owners pilled the dogs 12.1% of the doses and were unable to administer 0.3% of the doses.

Animal Safety Studies:

In a target animal safety study, PHENYLPRO was administered to 32 healthy male and female Beagle dogs at 0, 2, 6 and 10 mg/kg of body weight (0, 1, 3, and 5 times the recommended dose; 8 dogs per group) twice daily for 26 consecutive weeks. The most pronounced finding was a dose-dependent increase in blood pressure. Mean systolic blood pressure was increased in all PPA-treated groups compared to the control, but mean values for all 4 groups were within the normal range. Mean diastolic and mean MAP (mean arterial pressure) were higher in the 3X and 5X groups, and in the 1X males. Dogs in the 3X and 5X groups had more individual systolic, diastolic, and MAP values above the normal range than the control group dogs. A dose-dependent decrease in heart rate was observed in the 3X and 5X dogs. In the 0, 1, 3, and 5X groups, 5%, 34%, 44% and 40% of the total number of heart rates obtained from electrocardiograms for each group over the course of the study were below the normal range (70-120 beats per minute), with the lowest value being 51 bpm in 4 of the 1X group dogs. One dog in each of the 1X and 5X had an elevated heart rate between 150-180 beats per minute on at least 2 of the 13 physical exams. One dog in each of the 1X and 3X groups developed gallop heart sounds after treatment began that were noted in 12 of 13 and 6 of 13 physical exams respectively. Dogs in the PPA-treated group exhibited anxious/ restless behavior more frequently than the control group. One dog each in the 1X and 3X were responsible for the majority of the observations. A decline in mean body weight and body condition was observed in females in all 4 groups, including the control. One female in the 1X group lost 33% body weight. Vomiting and loose stool occurred in a dose-related fashion, and most of the vomiting episodes took place within 1 hour of dosing. Mean platelet counts were higher in at least one of the PPA treated groups, with individual values up to 1.4X the upper limit of normal (ULN) in the 3X and 5X group. The 3X and 5X groups had higher mean serum ALT values compared to the control. Mean ALT was within the normal range for all 4 groups. There were more dogs with ALT levels above the normal range in the 3X PPA treated compared to the control, but increased values were transient and less than 1.8X ULN. All dogs had ALT values in the normal range at the conclusion of the study.

In a separate tolerance study, 6 healthy female Beagle dogs were administered PHENYLPRO at 20 mg/kg body weight (10 times the recommended dose) twice daily for 21 consecutive days. Mean systolic blood pressure was increased in the 10X group compared to the control, but mean values were within the normal range for both groups. Mean diastolic pressures were above the normal range on days 7 and 21 for the 10X group, and day 14 for the control. The 10X dogs had hypertensive MAP values on days 7 and 21, whereas the control dog mean MAP values were in the normal range. There was a trend in 10X dogs for lower heart rates following initiation of PPA treatment. Four of 6 dogs in the 10X group had heart rates below the normal range on day 7, whereas none of the control dogs did. The 10X group dogs had increased hematocrit, hemoglobin, RBC counts, urine specific gravity, and water intake consistent with transient, sub-clinical dehydration that occurred shortly after PPA treatment was started. All 6 dogs in the 10X group vomited at least once during the treatment period, whereas only 1 of the control dogs did. Most of the vomiting episodes took place within 1 hour of dosing. Mean platelet counts were also higher in the 10X dogs on all 3 exam days; mean values were above the normal range on day 7, with individual values up to 1.5X ULN. The 10X group had a higher mean serum ALT value on day 7 than the control. Mean ALT values for both groups were in the normal range on all 3 exam days, but 2 dogs in the 10X group had ALT values up to 1.4X ULN on day 7; these elevated values were transient, and all dogs had normal ALT values on days 14 and 21.

For either study, there was no evidence of chronic hypertension-induced target organ damage; there were no clinical findings attributed to PPA on the ophthalmic exams, electrocardiogram evaluation, or gross necropsy and histopathology.

Storage:

Store at controlled room temperature 20-25°C (68-77°F), excursions permitted between 15-40°C (59-104°F)

How Supplied:

PHENYLPRO is scored and contains 25, 50 or 75 mg phenylpropanolamine hydrochloride per tablet. PHENYLPRO is packaged in bottles containing 60 or 180 tablets.

Approved by FDA under NADA # 141-324.

PHENYLPRO ® is a registered trademark of Pegasus Laboratories, Inc.

References:

^1 Watson R, et. al. Ephedra alkaloids inhibit platelet aggregation. Blood Coagulation and Fibrinolysis. 2010 21: 266-271

^2 Richter K. P., Ling G.V. Clinical response and urethral pressure profile changes after phenylpropanolamine in dogs with primary sphincter incompetence. JAVMA Vol 187 No. 6, September 15, 1985, 605-611.

^3 Scott, L., Leddy M., and Bernay F. Evaluation of phenylpropanolamine in the treatment of urethral sphincter mechanism incompetence in the bitch. J. Small Animal Pract. 2002; 43 (11): 493-6.

^4 Noel, S., et. al. Combined pharmacokinetic and urodynamic study of the effects of oral administration of phenylpropanolamine in female Beagle dogs. Vet Journal, 2010; 184 (2): 201-207.

^5 Hussain, M.A., Aungst, B.J., Lam, G., and Shefter, E. Phenylpropanolamine pharmacokinetics in dogs after intravenous, oral, and oral controlled-release doses. Biopharm Drug Dispos, Vol. 8, No. 5, September-October 1987, 497-505.